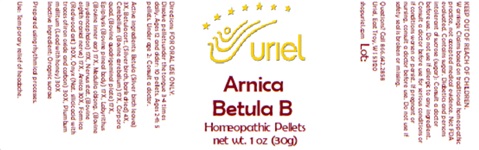 DRUG LABEL: Arnica Betula B
NDC: 48951-1117 | Form: PELLET
Manufacturer: Uriel Pharmacy Inc.
Category: homeopathic | Type: HUMAN OTC DRUG LABEL
Date: 20250627

ACTIVE INGREDIENTS: BETULA PUBESCENS LEAF 3 [hp_X]/1 1; BETULA PUBESCENS BARK 4 [hp_X]/1 1; BOS TAURUS CEREBELLUM 17 [hp_X]/1 1; BOS TAURUS BRAIN 17 [hp_X]/1 1; BOS TAURUS PINEAL GLAND 17 [hp_X]/1 1; SUS SCROFA EAR 17 [hp_X]/1 1; BOS TAURUS NERVE 17 [hp_X]/1 1; ARNICA MONTANA 30 [hp_X]/1 1; BIFENTHRIN 30 [hp_X]/1 1; LEAD 30 [hp_X]/1 1; HONEY 30 [hp_X]/1 1
INACTIVE INGREDIENTS: SUCROSE

Arnica Betula B

INDICATIONS AND USAGE

Directions: FOR ORAL USE ONLY.

DOSAGE AND ADMINISTRATION

Dissolve pellets under the tongue 3-4 times daily. Ages 12 and older: 10 pellets. Ages 2-11: 5 pellets. Under age 2: Consult a doctor.

ACTIVE INGREDIENT

Active Ingredients: Betula (Silver birch leaves) 3X, Betula cort. (Silver birch, bark dried) 4X, Cerebellum (Bovine cerebellum) 17X, Corpora quad. (Bovine Quadrigeminal plate) 17X, Epiphysis (Bovine pineal body) 17X, Labyrinthus (Bovine inner ear) 17X, Medulla oblong. (Bovine Myelencephalon 17X, Nervus stat. (Bovine eighth cranial nerve) 17X, Arnica 30X, Onyx (Nat. Silicic acid with traces of iron oxide and carbon) 30X, Plumbum mellitum (Lead with honey) 30X

Inactive Ingredient: Organic sucrose

Prepared using rhythmical processes.

PURPOSE

Use: Temporary relief of headache.

KEEP OUT OF REACH OF CHILDREN.

WARNINGS

Warnings: Claims based on traditional homeopathic practice, not accepted medical evidence. Not FDA evaluated. Contains sugar. Diabetics and persons intolerant of sucrose (sugar): Consult a doctor before use. Do not use if allergic to any ingredient. Consult a doctor before use for serious conditions or if conditions worsen or persist. If pregnant or nursing, consult a doctor before use. Do not use if safety seal is broken or missing.

Questions? Call 866.642.2858
Uriel, East Troy, WI 53120
shopuriel.com Lot: